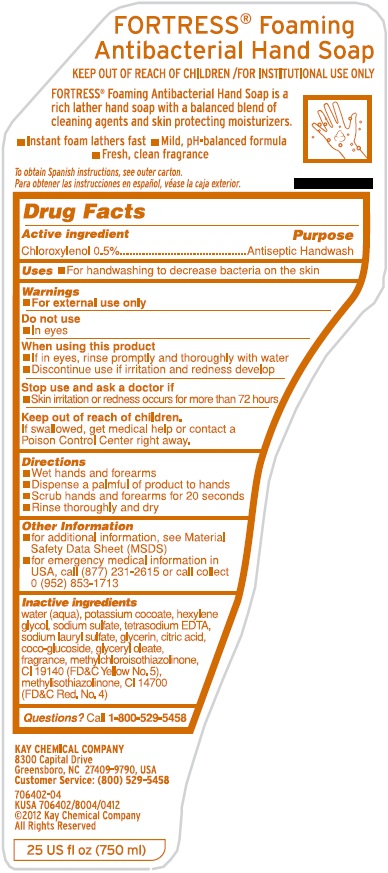 DRUG LABEL: Fortress Foaming Antibacterial HandSoap
NDC: 47593-694 | Form: SOLUTION
Manufacturer: Ecolab Inc.
Category: otc | Type: HUMAN OTC DRUG LABEL
Date: 20251217

ACTIVE INGREDIENTS: CHLOROXYLENOL 5 mg/1 mL
INACTIVE INGREDIENTS: WATER; POTASSIUM COCOATE; HEXYLENE GLYCOL; SODIUM SULFATE; EDETATE SODIUM; SODIUM LAURYL SULFATE; GLYCERIN; ANHYDROUS CITRIC ACID; COCO GLUCOSIDE; GLYCERYL OLEATE; METHYLCHLOROISOTHIAZOLINONE; METHYLISOTHIAZOLINONE; FD&C YELLOW NO. 5; FD&C RED NO. 4

Drug Facts

Active ingredient

Chloroxylenol 0.5%

Purpose

Antiseptic Handwash

Uses

- For handwashing to decrease bacteria on the skin.

Warnings

- For external use only

Do not use

- In eyes

When using this product

- If in eyes, rinse promptly and thoroughly with water
- Discontinue use if irritation and redness develop

Stop use and ask a doctor if

- Skin irritation or redness occurs for more than 72 hours

Keep out of reach of children.

If swallowed, get medical help or contact a Poison Control Center right away.

Directions

- Wet hands and forearms
- Dispense a palmful of product to hands
- Scrub hands and forearms for 20 seconds
- Rinse thoroughly and dry

Other Information

- for additional information, see Material Safety Data Sheet (MSDS)
- for emergency medical information in USA, call (877) 231-2615 or call collect 0 (952) 853-1713

INACTIVE INGREDIENT

Inactive ingredients: water (aqua), potassium cocoate, hexylene glycol, sodium sulfate, tetrasodium EDTA, sodium lauryl sulfate, glycerin, citric acid, coco-glucoside, glyceryl oleate, fragrance, methychloroisothiazolinone, CI 19140 (FD&C Yellow No. 5), methylisothiazolinone, CI 14700 (FDC Red No. 4)

Questions? Call 1-800-529-5458

Principal display panel and representative label

FORTRESS® Foaming Antibacterial Hand Soap

KEEP OUT OF REACH OF CHILDREN/FOR INSTITUTIONAL USE ONLY

FORTRESS® Foaming Antibacterial Hand Soap is a rich lather hand soap with a balanced blend of cleaning agents and skin protecting moisturizers.

- Instant foam lathers fast • Mild, pH-balanced formula
- Fresh, clean fragrance

To obtain Spanish instructions, see outer carton.

Para obtener las instrucciones en español, véase la caja exterior.

KAY CHEMICAL COMPANY

8300 Capital Drive

Greensboro, NC 27409-3790, USA

Customer Service: (800) 529-5458

706402-04

KUSA 706402/8004/0412

©2012 Kay Chemical Company

All Rights Reserved

25 US fl OZ (750 ml)